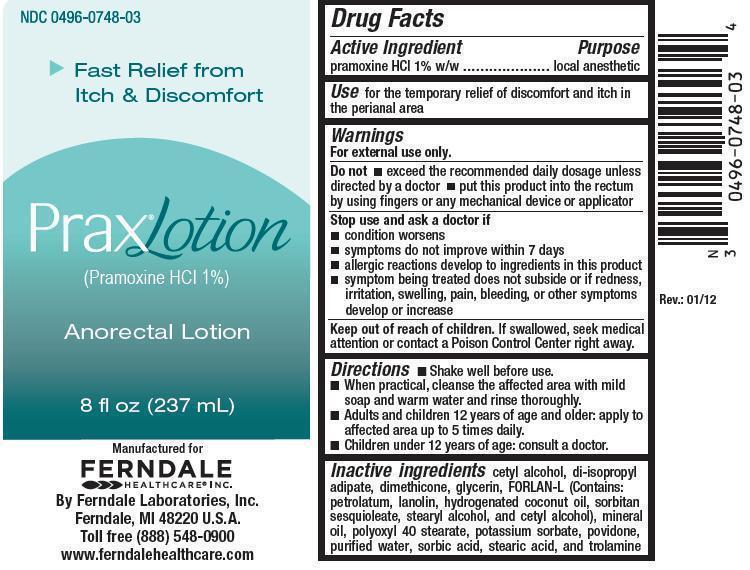 DRUG LABEL: PRAX
NDC: 0496-0748 | Form: LOTION
Manufacturer: Ferndale Laboratories, Inc.
Category: otc | Type: HUMAN OTC DRUG LABEL
Date: 20241217

ACTIVE INGREDIENTS: PRAMOXINE HYDROCHLORIDE 10 mg/1 mL
INACTIVE INGREDIENTS: CETYL ALCOHOL; DIISOPROPYL ADIPATE; DIMETHICONE; GLYCERIN; PETROLATUM; LANOLIN; HYDROGENATED COCONUT OIL; SORBITAN SESQUIOLEATE; STEARYL ALCOHOL; MINERAL OIL; POLYOXYL 40 STEARATE; POTASSIUM SORBATE; POVIDONE; WATER; SORBIC ACID; STEARIC ACID; TROLAMINE

Prax® Lotion (Pramoxine HCl 1%)

Active Ingredient

pramoxine HCl 1% w/w

Purpose

local anesthetic

Use

for the temporary relief of discomfort and itch in the perianal area

Warnings

For external use only.

Do not

- exceed the recommended daily dosage unless directed by a doctor
- put this product into the rectum by using fingers or any mechanical device or applicator

Stop use and ask a doctor if

- condition worsens
- symptoms do not improve within 7 days
- allergic reactions develop to ingredients in this product
- symptom being treated does not subside or if redness, irritation, swelling, pain, bleeding, or other symptoms develop or increase

Keep out of reach of children.

If swallowed, seek medical attention or contact a Poison Control Center right away.

Directions

- Shake well before use.
- When practical, cleanse the affected area with mild soap and warm water and rinse thoroughly.
- Adults and children 12 years of age and older: apply to affected area up to 5 times daily.
- Children under 12 years of age: consult a doctor.

Inactive Ingredients

cetyl alcohol, di-isopropyl adipate, dimethicone, glycerin, FORLAN-L (Contains: petrolatum, lanolin, hydrogenated coconut oil, sorbitan sesquioleate, stearyl alcohol, and cetyl alcohol), mineral oil, polyoxyl 40 stearate, potassium sorbate, povidone, purified water, sorbic acid, stearic acid, and trolamine

Package Label

Manufactured for
Ferndale Healthcare® Inc.
By Ferndale Laboratories, Inc.
Ferndale, MI 48220 U.S.A.
Toll Free (888) 548-0900
www.ferndalehealthcare.com

8 fl oz (237 mL) NDC 0496-0748-03